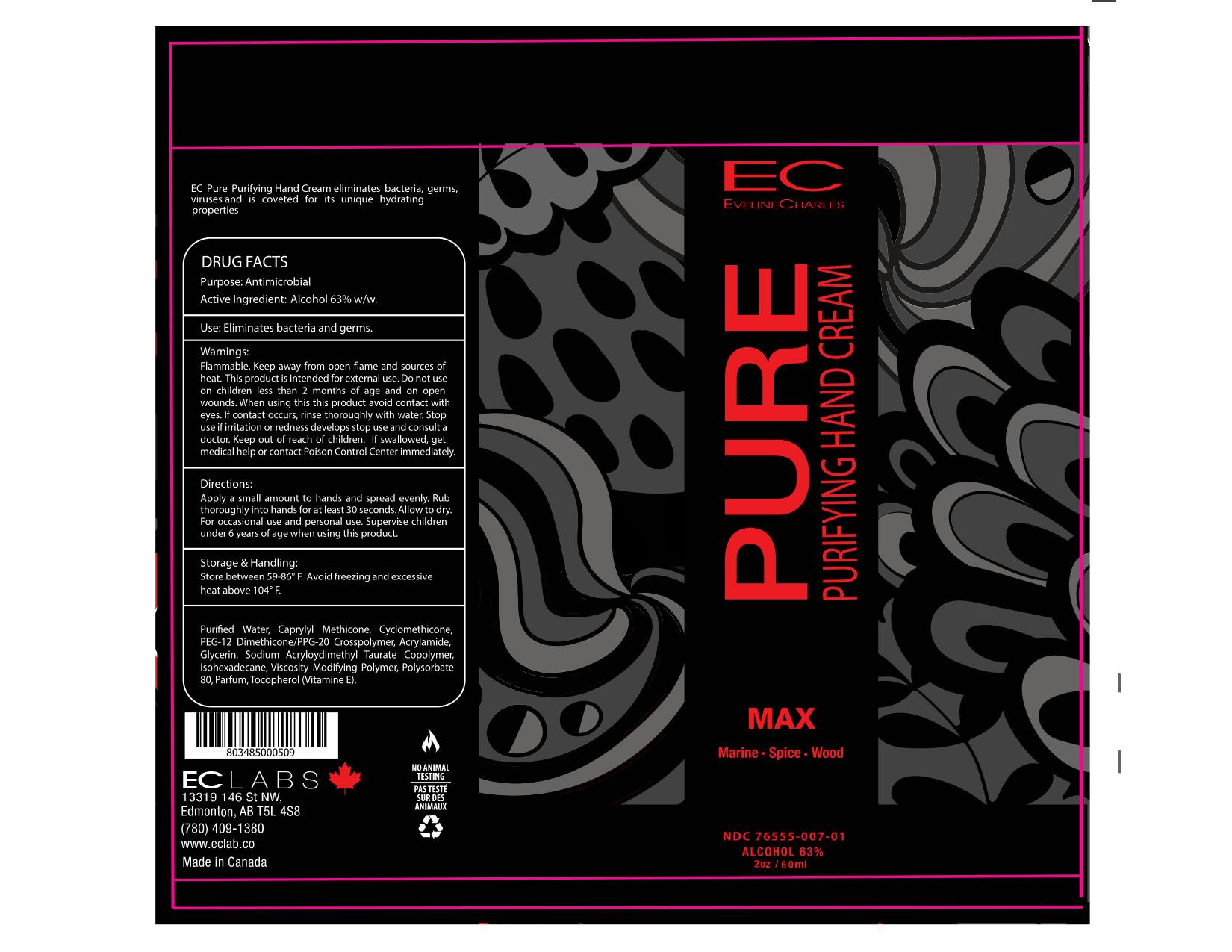 DRUG LABEL: EvelineCharles PURE Purifying Hand Cream Max
NDC: 76555-007 | Form: CREAM
Manufacturer: EC Labs Inc.
Category: otc | Type: HUMAN OTC DRUG LABEL
Date: 20211028

ACTIVE INGREDIENTS: ALCOHOL 37.8 g/60 g
INACTIVE INGREDIENTS: GLYCERIN 0.29 g/60 g; PEG/PPG-18/12 DIMETHICONE 5.1 g/60 g; WATER 13.14 g/60 g; SODIUM ACRYLOYLDIMETHYLTAURATE 1.74 g/60 g; AMMONIUM ACRYLOYLDIMETHYLTAURATE, DIMETHYLACRYLAMIDE, LAURYL METHACRYLATE AND LAURETH-4 METHACRYLATE COPOLYMER, TRIMETHYLOLPROPANE TRIACRYLATE CROSSLINKED (45000 MPA.S) 0.79 g/60 g; TOCOPHEROL 0.06 g/60 g; 2,6-DIMETHYL-5-HEPTENAL 0.0012 g/60 g; 3-CARENE 0.0012 g/60 g; DIHYDROMYRCENOL (MIXED ISOMERS) 0.0036 g/60 g; ETHYL LINALOOL 0.0012 g/60 g; CEDRAMBER 0.0012 g/60 g; CYMENE 0.0012 g/60 g; LINALOOL, (+/-)- 0.0012 g/60 g; CYCLOMETHICONE 1.02 g/60 g; TETRAMETHYL ACETYLOCTAHYDRONAPHTHALENES 0.0072 g/60 g; .BETA.-PINENE 0.0012 g/60 g; GERANIOL 0.0012 g/60 g; METHYL IONONES 0.0012 g/60 g; .ALPHA.-PINENE 0.0012 g/60 g; PENTADECALACTONE 0.0012 g/60 g; BENZYL SALICYLATE 0.0024 g/60 g; DIHYDRO PENTAMETHYLINDANONE 0.0024 g/60 g; COUMARIN 0.0012 g/60 g; LINALYL ACETATE 0.0024 g/60 g; BOURGEONAL 0.0012 g/60 g; 2-TERT-BUTYLCYCLOHEXYL ACETATE 0.0024 g/60 g; LIMONENE, (+)- 0.0024 g/60 g; .GAMMA.-TERPINENE 0.0012 g/60 g; METHYL 3-METHYLORSELLINATE 0.0012 g/60 g; ALLYL CYCLOHEXANEBUTYRATE 0.0012 g/60 g; .BETA.-CITRONELLOL, (R)- 0.0012 g/60 g; 3-(3,4-METHYLENEDIOXYPHENYL)-2-METHYLPROPANAL 0.0024 g/60 g; AMBREIN 0.0012 g/60 g; CYCLOHEXANEPROPANOL, 2,2,6-TRIMETHYL-.ALPHA.-PROPYL- 0.0012 g/60 g

Eveline Charles Pure Purifying Hand Cream Max

This is a hand sanitizer manufactured according to the Temporary Policy for Preparation of Certain Alcohol-Based Hand Sanitizer Products During the Public Health Emergency (CoViD-19); Guidance for Industry.

The hand sanitizer is manufactured using only the following United States Pharmacopoeia (USP) grade ingredients in the preparation of the product (percentage in final product formulation) consistent with World Health Organization (WHO) recommendations:

1. Alcohol (ethanol) (USP or Food Chemical Codex (FCC) grade) (80%, volume/volume (v/v)) in an aqueous solution denatured according to Alcohol and Tobacco Tax and Trade Bureau regulations in 27 CFR part 20.
2. Glycerol (1.45% v/v).
3. Hydrogen peroxide (0.125% v/v).
4. Sterile distilled water or boiled cold water.

The firm does not add other active or inactive ingredients. Different or additional ingredients may impact the quality and potency of the product.

Active Ingredient(s)

Alcohol 63% w/w. Purpose: Antimicrobial

Purpose

Antimicrobial, Purifying Hand Cream

Use

Eliminates bacteria and germs.

Warnings

Flammable. Keep away from open flame and sources of heat. This product is intended for external use only.

Do not use in children less than 2 months of age and on open skin wounds.

When using this product avoid contact with eyes. If contact occurs, rinse thoroughly with water.

Stop use if irritation or redness develops and consult a doctor.

Keep out of reach of children. If swallowed, get medical help or contact a Poison Control Center right away.

Directions

Apply a small amount to hands and spread evenly.

Rub thoroughly into hands for at least 30 seconds.

Other information

- Store between 15-30C (59-86F)
- Avoid freezing and excessive heat above 40C (104F)

Inactive ingredients

glycerin, purified water USP

Package Label - Principal Display Panel

60g NDC: 76555-007-01